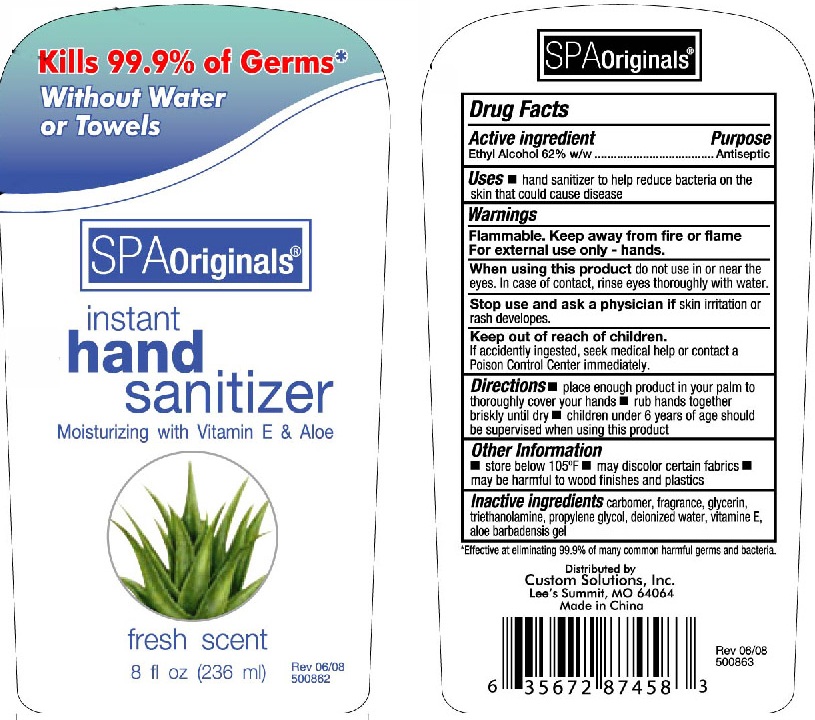 DRUG LABEL: Spa Originals Instant Hand Sanitizer
NDC: 76405-010 | Form: LIQUID
Manufacturer: Custom Solutions, Inc.
Category: otc | Type: HUMAN OTC DRUG LABEL
Date: 20110923

ACTIVE INGREDIENTS: ALCOHOL 62 mL/100 mL
INACTIVE INGREDIENTS: GLYCERIN; TROLAMINE; PROPYLENE GLYCOL; WATER; ALPHA-TOCOPHEROL; ALOE VERA FLOWER

Spa Originals Instant Hand Sanitizer

Active Ingredient

Ethyl Alcohol 62% w/w

Purpose

Antiseptic

Uses

Hand sanitizer to help reduce bacteria on the skin that could cause disease

Warnings

Flammable. Keep away from fire or flame

For external use only - hands.

When using this product

do not use in or near the eyes. In case of contact, rinse eyes thoroughly with water.

Stop use and ask a physician

If skin irritation or rash develops.

Keep out of reach of children.

If accidentally ingested, seek medical help or contact a Poison Control Center immediately.

Directions

place enough product in your palm to thoroughly cover your hands.

rub hands together briskly until dry

children under 6 years of age should be supervised when using this product.

Other information

store below 105F

may discolor certain fabircs

may be harmful to wood finishes and plastics

Inactive Ingredients

carbomer, fragrance, glycerin, triethanolamine, propylene glycol, deionized water, vitamin E, aloe barbadensis gel

*Effective at eliminating 99.9% of many harmful germs and bacterial

Distributed by:

Custom Solutions, Inc.
Lee's Summit, MO 64064
Made in China

PACKAGE LABEL

Kills 99,9% of germs*
without water or towels

SPA Originals

instant hand sanitizer

Moisturizing with Vitamin E and Aloe

Fresh Scent

8fl oz (236mL)